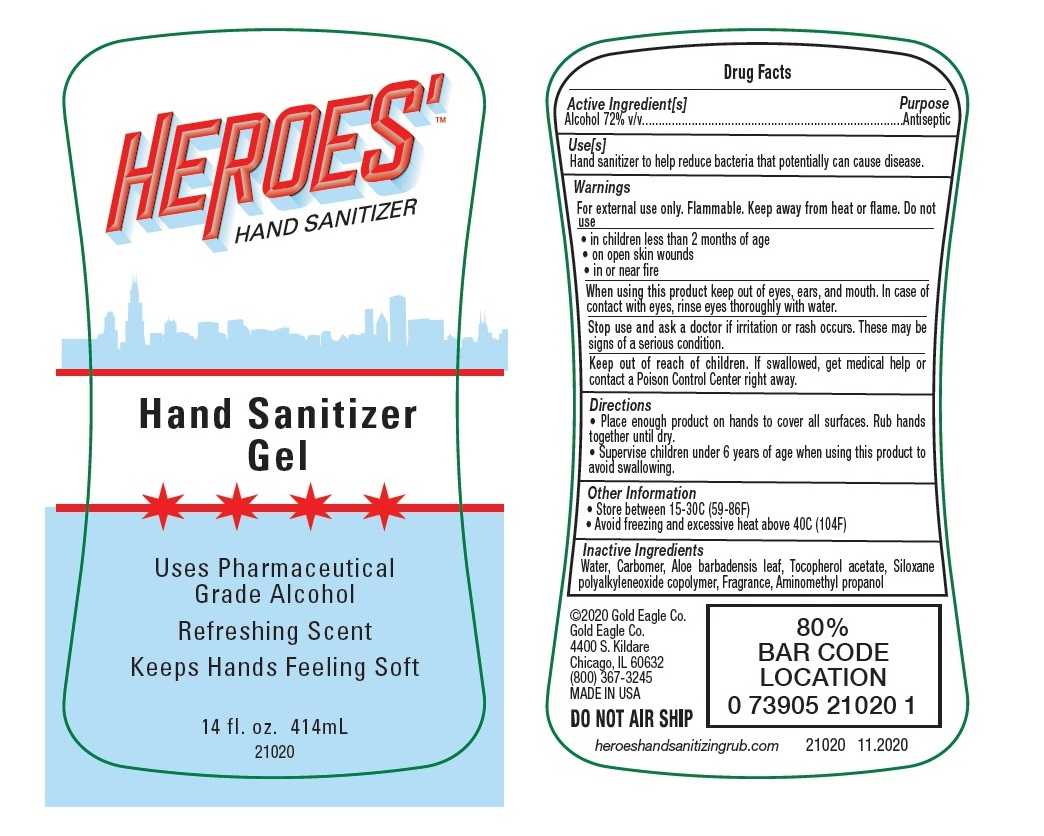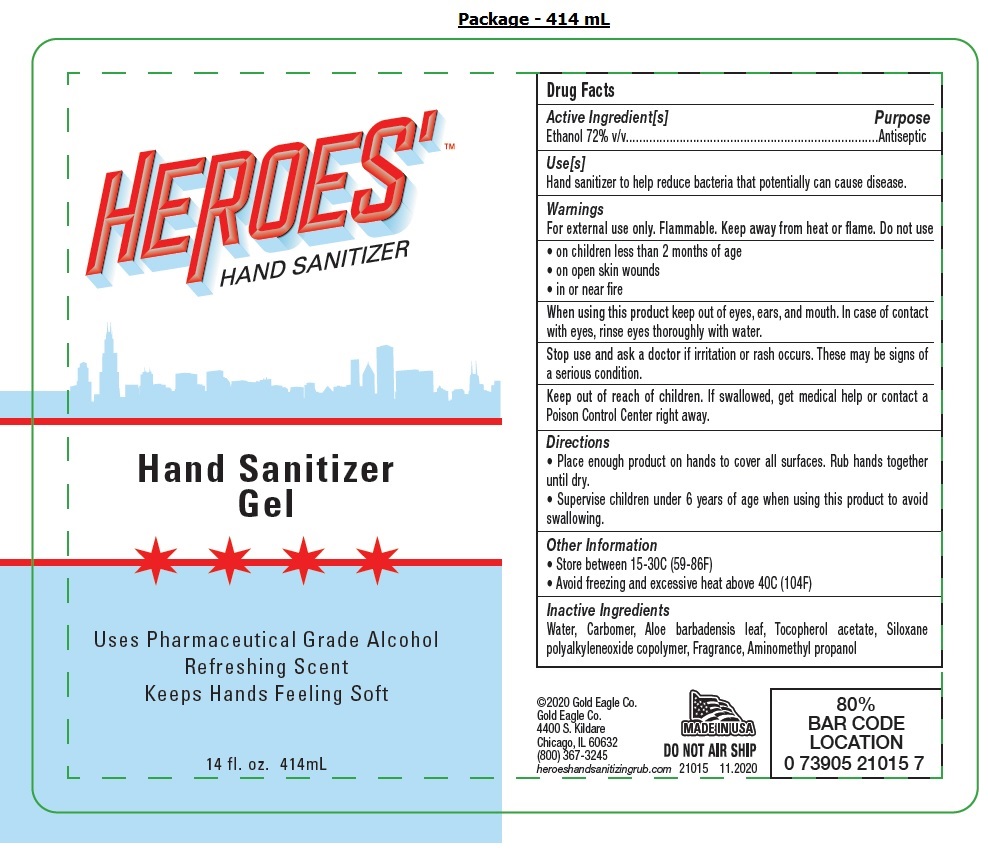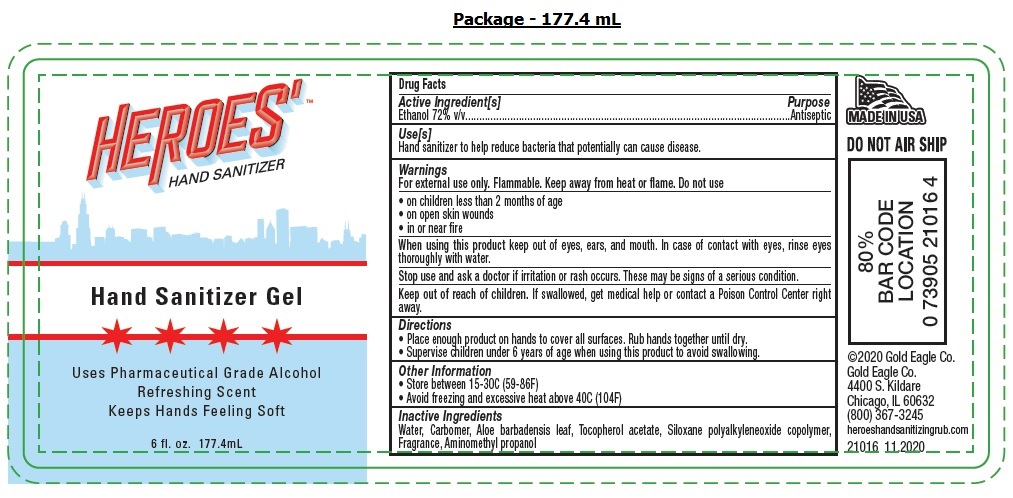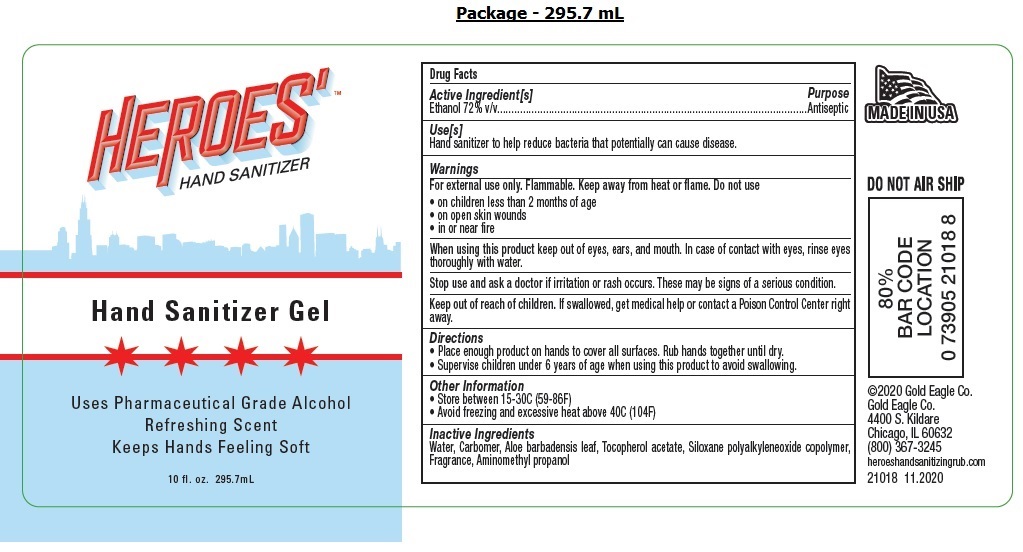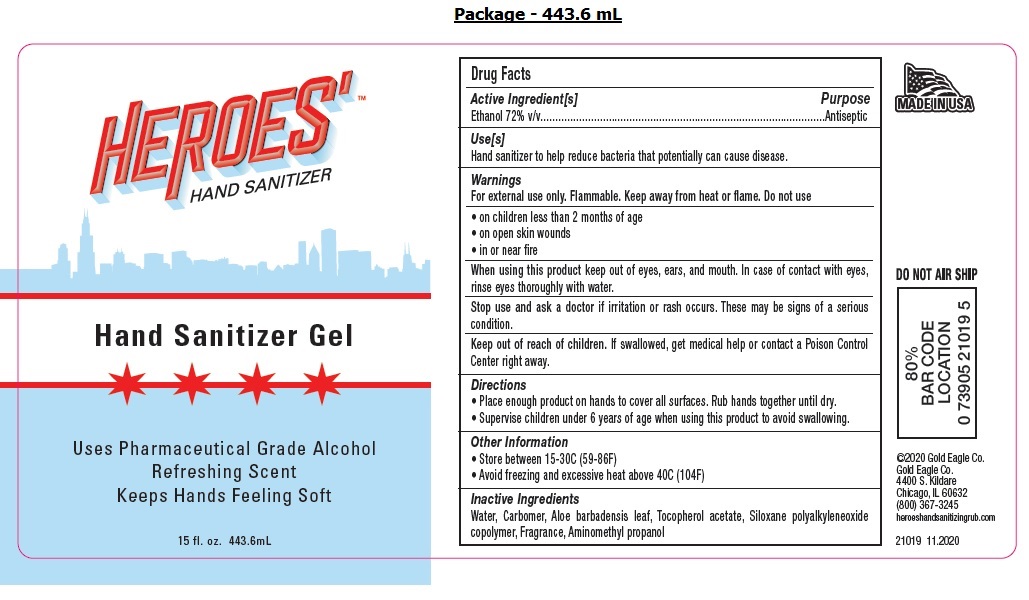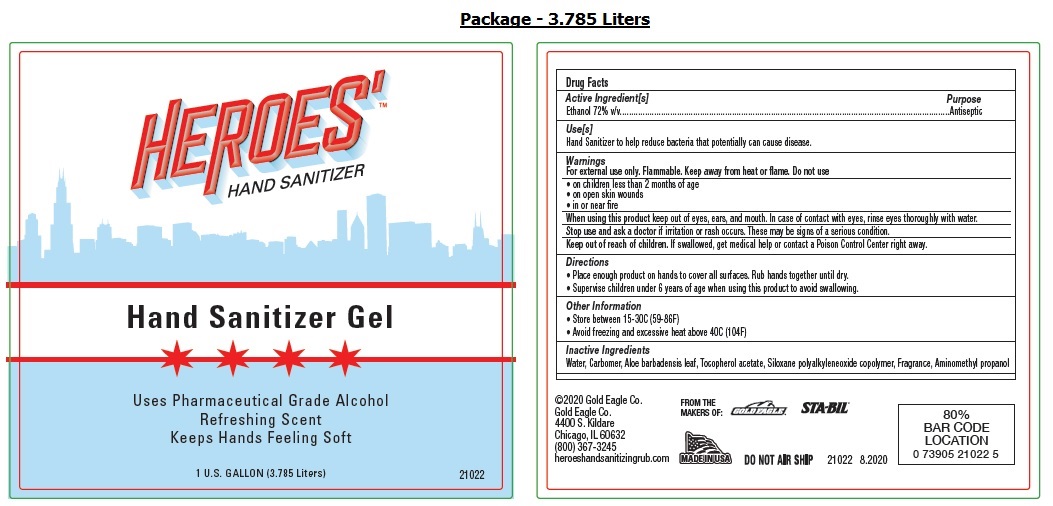 DRUG LABEL: HEROES Hand Sanitizer Gel
NDC: 78007-114 | Form: GEL
Manufacturer: Gold Eagle Co.
Category: otc | Type: HUMAN OTC DRUG LABEL
Date: 20201116

ACTIVE INGREDIENTS: ALCOHOL 72 mL/100 mL
INACTIVE INGREDIENTS: WATER; CARBOMER HOMOPOLYMER, UNSPECIFIED TYPE; ALOE VERA LEAF; .ALPHA.-TOCOPHEROL ACETATE; PEG-10 DIMETHICONE (600 CST); AMINOMETHYLPROPANOL

HEROES' TM Hand Sanitizer Gel

Active Ingredient[s]

Ethanol 72% v/v

Purpose

Antiseptic

Use[s]

Hand sanitizer to help reduce bacteria that potentially can cause disease.

Warnings

For external use only. Flammable. Keep away from heat or flame. Do not use

• on children less than 2 months of age
• on open skin wounds
• in or near fire
When using this product keep out of eyes, ears, and mouth. In case of contact with eyes, rinse eyes thoroughly with water.
Stop use and ask a doctor if irritation or rash occurs. These may be signs of a serious condition.

Keep out of reach of children. If swallowed, get medical help or contact a Poison Control Center right away.

Directions

• Place enough product on hands to cover all surfaces. Rub hands together until dry.
• Supervise children under 6 years of age when using this product to avoid swallowing.

Other Information

• Store between 15-30C (59-86F)
• Avoid freezing and excessive heat above 40C (104F)

Inactive Ingredients

Water, Carbomer, Aloe barbadensis leaf, Tocopherol acetate, Siloxane polyalkyleneoxide copolymer, Fragrance, Aminomethyl propanol

Uses Pharmaceutical Grade Alcohol
Refreshing Scent
Keeps Hands Feeling Soft

©2020 Gold Eagle Co.
Gold Eagle Co.
4400 S. Kildare
Chicago, IL 60632
(800) 367-3245
heroeshandsanitizingrub.com

MADE IN USA

DO NOT AIR SHIP